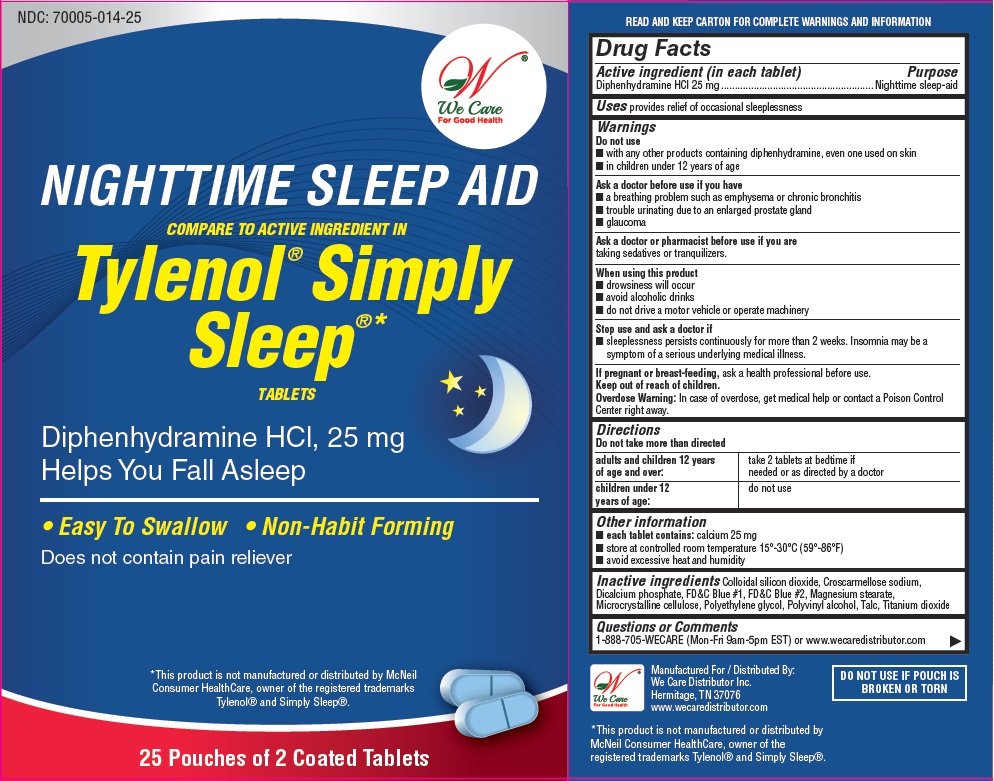 DRUG LABEL: Nighttime Sleep Aid
NDC: 70005-014 | Form: TABLET
Manufacturer: We Care Distributor Inc
Category: otc | Type: HUMAN OTC DRUG LABEL
Date: 20160223

ACTIVE INGREDIENTS: DIPHENHYDRAMINE HYDROCHLORIDE 25 mg/1 1
INACTIVE INGREDIENTS: SILICON DIOXIDE; CROSCARMELLOSE SODIUM; ANHYDROUS DIBASIC CALCIUM PHOSPHATE; MAGNESIUM STEARATE; CELLULOSE, MICROCRYSTALLINE; TITANIUM DIOXIDE; POLYVINYL ALCOHOL; POLYETHYLENE GLYCOL 400; TALC; FD&C BLUE NO. 1; FD&C BLUE NO. 2

Drug Facts

Active ingredient (in each tablet)

Diphenhydramine HCl 25 mg

Purpose

Nighttime sleep-aid

Uses

provides relief of occasional sleeplessness

Warnings

Do not use

- with any other products containing diphenhydramine, even one used on skin
- in children under 12 years of age

Ask a doctor before use if you have

- a breathing problem such as emphysema or chronic bronchitis
- trouble urinating due to an enlarged prostate gland
- glaucoma

Ask a doctor or pharmacist before use if you are

taking sedatives or tranquilizers

When using this product

- drowsiness may occur
- avoid alcoholic drinks
- do not drive a motor vehicle or operating a machinery

Stop use and ask a doctor if

sleeplessness persists continuously for more than 2 weeks. Insomnia may be a symptom of a serious underlying medical illness.

If pregnant or breast-feeding

ask a health professional before use.

Keep out of reach of children.

In case of overdose, get medical help or contact a Poison Control Center right away. (1-800-222-1222)

Directions

- do not take more than directed
- adults and children 12 years of age and over - take 2 tablets at bedtime if needed or as directed by a doctor
- children under 12 years of age: do not use

Other Information

- each caplet contains; calcium 25 mg
- store at controlled room temperature 15°-30°C (59°-86°F)
- avoid excessive heat and humidity

Inactive Ingredients

Colloidal silicon dioxide, Croscarmellose sodium, Dicalcium phosphate, FD&C Blue #1, FD&C Blue #2, Magnesium stearate, Microcrystalline cellulose, Polyethylene glycol, Polyvinyl alcohol, Talc, Titanium dioxide

Questions or comments?

Call: 1-800-705-WECARE (Mon-Fri 9am-5pm EST) or www.wecaredistributor.com